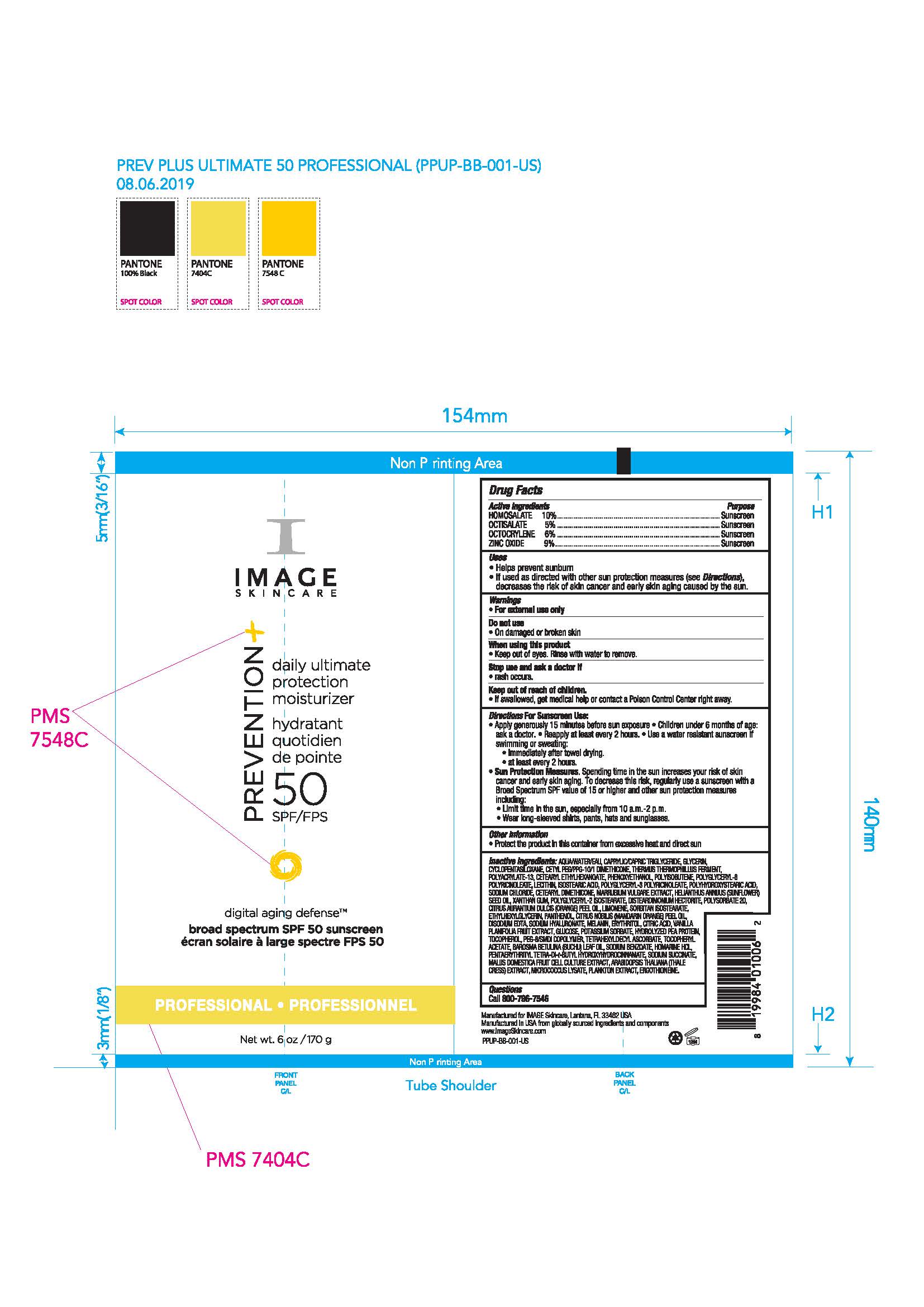 DRUG LABEL: Image Prevention Plus Professional Ultimate Protection Moisturizer SPF50
NDC: 60232-1026 | Form: CREAM
Manufacturer: Swiss-American CDMO, LLC
Category: otc | Type: HUMAN OTC DRUG LABEL
Date: 20231106

ACTIVE INGREDIENTS: HOMOSALATE 110 g/1000 g; OCTISALATE 50 g/1000 g; OCTOCRYLENE 60 g/1000 g; ZINC OXIDE 90 g/1000 g
INACTIVE INGREDIENTS: WATER; MEDIUM-CHAIN TRIGLYCERIDES; GLYCERIN; CYCLOMETHICONE 5; CETYL PEG/PPG-10/1 DIMETHICONE (HLB 1.5); THERMUS THERMOPHILUS; CETEARYL ETHYLHEXANOATE; PHENOXYETHANOL; POLYISOBUTYLENE (1000 MW); LECITHIN, SOYBEAN; ISOSTEARIC ACID; POLYHYDROXYSTEARIC ACID (2300 MW); SODIUM CHLORIDE; CETYL DIMETHICONE 150; MARRUBIUM VULGARE; SUNFLOWER OIL; DISTEARDIMONIUM HECTORITE; POLYSORBATE 20; ORANGE OIL; LIMONENE, (+/-)-; SORBITAN ISOSTEARATE; ETHYLHEXYLGLYCERIN; PANTHENOL; EDETATE DISODIUM; HYALURONIC ACID; ERYTHRITOL; ANHYDROUS CITRIC ACID; VANILLA BEAN; ANHYDROUS DEXTROSE; POTASSIUM SORBATE; TOCOPHEROL; PEG-8/SMDI COPOLYMER; TETRAHEXYLDECYL ASCORBATE; .ALPHA.-TOCOPHEROL ACETATE; AGATHOSMA BETULINA LEAF OIL; SODIUM BENZOATE; HOMARINE HYDROCHLORIDE; PENTAERYTHRITOL TETRAKIS(3-(3,5-DI-TERT-BUTYL-4-HYDROXYPHENYL)PROPIONATE); SODIUM SUCCINATE ANHYDROUS; MALUS DOMESTICA WHOLE; MICROCOCCUS LUTEUS; ERGOTHIONEINE

Image Prevention Plus Professional Ultimate Protection Moisturizer SPF50

Warnings

For external use only. Do not use on damaged or broken skin. When using this product keep out of eyes. Rinse with water to remove. Stop use and ask a doctor if rash occurs. If swallowed, get medical help or contact a Poison Control Center right away.

Keep out of Reach of Children

Active Ingredients

Homosalate 10% Sunscreen

Octisalate 5% Sunscreen

Octocrylene 6% Sunscreen

Zinc Oxide 9% Sunscreen

Uses

Helps prevent sunburn. If used as directed with other sun protection measures (see Directions), decreases the risk of skin cancer and early skin aging caused by the sun.

Uses

Helps prevent sunburn. If used as directed with other sun protection measures (see Directions), decreases the risk of skin cancer and early skin aging caused by the sun.

Directions For Sunscreen Use

Apply generously 15 minutes before sun exposure. Children under 6 months of age: ask a doctor. Reapply at least every 2 hours. Use a water resistant sunscreen if swimming or sweating. Immediately after towel drying. At least every 2 hours. Sun Protection Measures. Spending time in the sun increases your risk of skin cancer and early skin aging. To decrease this risk, regularly use a sunscreen with a Broad Spectrum SPF value of 15 or higher and other sun protection measures including: limit time in the sun, especially from 10am to 2pm, wear long-sleeved shirts, pants, hats and sunglasses.

Other Information

Protect the product in this container from excessive heat and direct sun.

Inactive Ingredients

water, caprylic/capric triglyceride, glycerin, cyclopentasiloxane, cetyl PEG/PPG-10/1 dimethicone, thermus thermophillus ferment, polyacrylate-13, cetearyl ethylhexanoate, phenoxyethanol, polyisobutene, polyglyceryl-6 polyricinoleate, lecithin, isostearic acid, polyglyceryl-3 polyricinoleate, polyhydroxystearic acid, soidum chloride, cetearyl dimethicone, marrubium vulgare extract, helianthus annus (sunflower) see oil, disteardimonium hectorite, polysorbate 20, citrus aurantum dulcis (orange) peel oil, limonene, sorbitan isostearate, ethylhexylglycerin, panthenol, citrus nobils (mandarin orange) peel oil, disodium EDTA, sodium hyaluronate, melanin, erythritol, citric acid, vanilla planifolia fruit extract, glucose, potassium sorbate, hydrolyzed pea protein, tocopherol, PEG-8/SMDI copolymer, tetrahexyldecyl ascorbate, tocopheryl acetate, barosma betuuna (buchu) leaf oil, soidum benzoate, homarine HCL, pentaerythrityl tetra-di-t-butylhydroxyhydrocinnamate, sodium succinate, malus domestica fruit cell culture extract, arabidopsis thaliana (thale cress) extract, micrococcus lysate, plankton extract, ergothioneine

Questions

Questions: call 800-796-7546